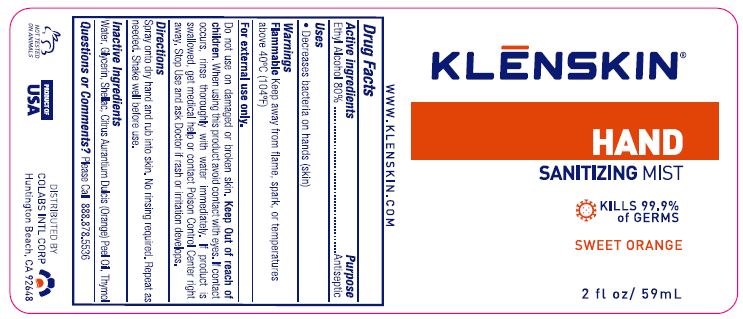 DRUG LABEL: KLENSKIN HAND SANITIZING MIST
NDC: 61369-401 | Form: SPRAY
Manufacturer: CoLabs Intl. Corp
Category: otc | Type: HUMAN OTC DRUG LABEL
Date: 20240115

ACTIVE INGREDIENTS: ALCOHOL 80 mL/100 mL
INACTIVE INGREDIENTS: GLYCERIN; SHELLAC; ORANGE OIL; THYMOL; WATER

COLABS - KLENSKIN HAND SANITIZING MIST (80% ETHYL ALCOHOL)

ACTIVE INGREDIENTS

ETHYL ALCOHOL 80% W/W

PURPOSE

ANTISEPTIC

USES

- Decreases bacteria on hands (skin)
- Recommended for repeated use

WARNINGS

Flammable Keep away from flame, spark, or temperatures above 40°C (104°F)

For external use only.

Do not use on damaged or broken skin.

KEEP OUT OF REACH OF CHILDREN.

When using this product avoid contact with eyes. If contact occurs, rinse thoroughly with water immediately. If product is
swallowed, get medical help or contact Poison Control Center right away. Stop Use and ask Doctor if rash or irritation develops.

DIRECTIONS

Spray onto dry hand and rub into skin. No rinsing required. Repeat as needed. Shake well before use.

INACTIVE INGREDIENTS

Water, Glycerin, Shellac, Citrus Aurantium Dulcis (Orange) Peel Oil, Thymol

QUESTIONS OR COMMENTS?

PLEASE CALL TOLL FREE 888.878.5536